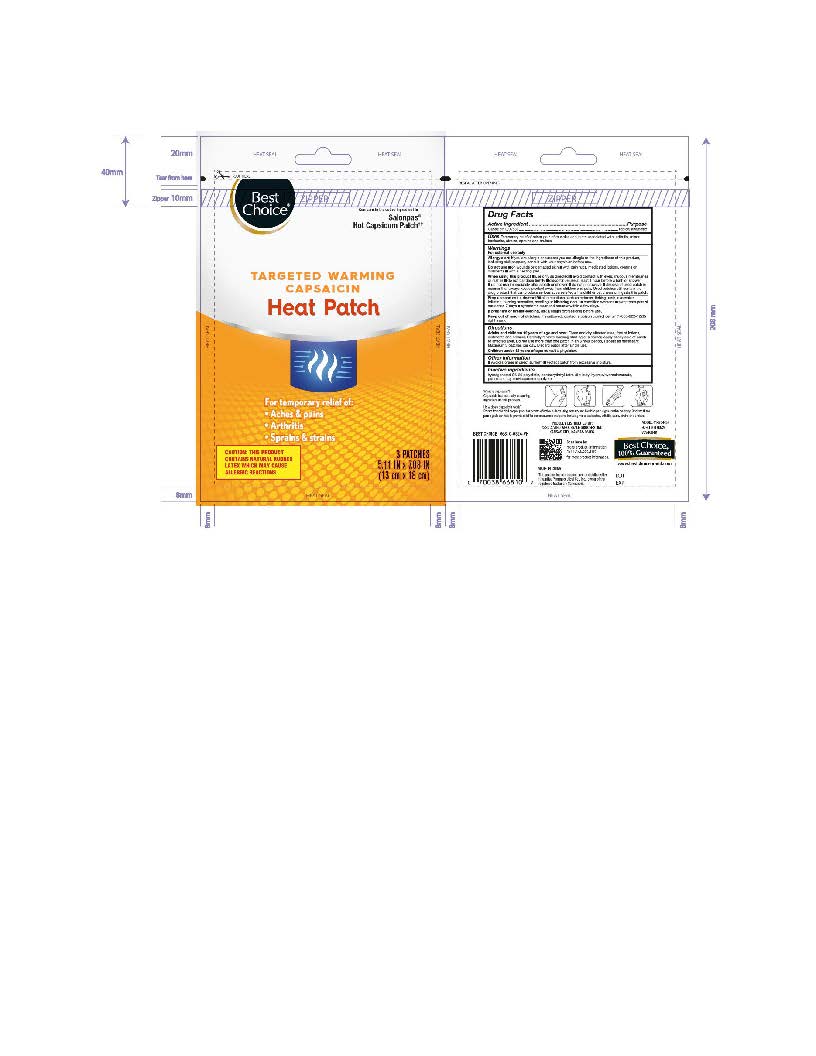 DRUG LABEL: Best Choice Targeted Warming Capsaicin Heat Patch
NDC: 63941-691 | Form: PATCH
Manufacturer: Valu Merchandisers Company
Category: otc | Type: HUMAN OTC DRUG LABEL
Date: 20260118

ACTIVE INGREDIENTS: CAPSICUM 0.025 g/100 g
INACTIVE INGREDIENTS: HYDROGENATED C6-20 POLYOLEFIN (100 CST); NATURAL LATEX RUBBER; PENTAERYTHRITOL TETRAKIS(3-(3,5-DI-TERT-BUTYL-4-HYDROXYPHENYL)PROPIONATE); LIQUID PETROLEUM; STYRENE/ISOPRENE COPOLYMER (28:72; 210000 MW)

Best Choice Targeted Warming Capsaicin Heat Patch

Active ingredient

Capsaicin 0.025%

Purpose

Topical analgesic

Uses

Temporary relief of minor pain of muscles and joints associated with: arthritis, minor backache, strains, sprains and bruises

Warnings

For external use only

Do not use

- on wounds or damaged skin
- with pain rubs, medicated lotions, creams or ointments
- with a heating pad.

When using this product

- use only as directed
- avoid contact with the eyes, mucous membranes or rashes
- do not bandage tightly
- discontinue use at least 1 hour before a bath or shower
- do not use immediately after a bath or shower
- do not microwave
- dispose of used patch in manner that always keeps product away from children and pets. Used patches still contain the drug product that can produce serious adverse effects if a child or pet chews or ingests this patch.

Stop use and ask a doctor if

- skin reactions such as redness, itching, rash, excessive irritation, burning sensation, swelling or blistering occur
- condition worsens
- symptoms persist more than 7 days
- symptoms clear and reoccur within a few days.

If pregnant or breast-feeding,

ask a health professional before use.

Keep out of reach of children.

If swallowed, contact a poison control center (1-800-222-1222) right away.

Allergy alert:

If you are allergic or suspect you are allergic to the ingredients of this product, including chilli peppers, consult with your physician before use.

Directions

Adults and children 12 years of age and over: Clean and dry affected area, free of lotions, oitments and creams. Carefully remove backing starting at a corner. Apply sticky side of patch to affected area. Do not use more than one patch in an 8 hour period. Repeat as necessary. Maximum 3 patches per day. Discard patch after single use.

Children under 12 years of age:consult a physician.

Other information

- Avoid storage in direct sunlight
- Protect patch from excessive moisture.

Inactive ingredients

hydrogenated C6-20 polyolefin, pentaerythrityl tetra-di-t-butyl hydroxyhydrocinnamate, petroleum, styrene/isoprene copolymer

Scan here for more product information.

Call 1-844-292-1112 for more product information.